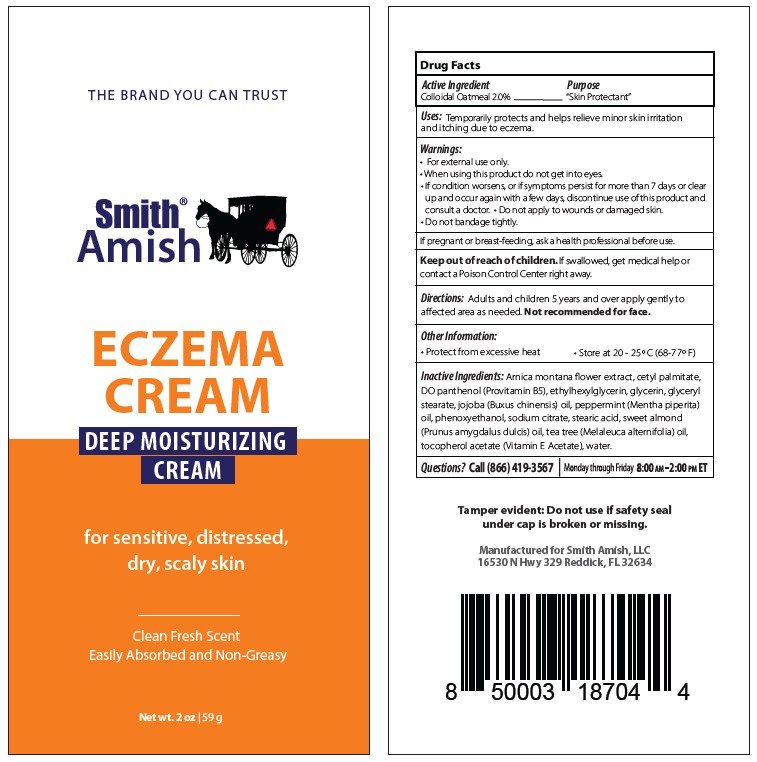 DRUG LABEL: ECZEMA
NDC: 72609-704 | Form: CREAM
Manufacturer: Smith Amish, LLC
Category: otc | Type: HUMAN OTC DRUG LABEL
Date: 20251212

ACTIVE INGREDIENTS: OATMEAL 1.25 g/100 g
INACTIVE INGREDIENTS: ALMOND OIL; JOJOBA OIL; GLYCERYL MONOSTEARATE; PEPPERMINT OIL; .ALPHA.-TOCOPHEROL; ARNICA MONTANA WHOLE; CETYL PALMITATE; SODIUM CITRATE; STEARIC ACID; TEA TREE OIL; WATER; GLYCERIN; PHENOXYETHANOL; PANTHENOL

Smith Amish Eczema Cream (2oz) - 72609-704-02; Smith Amish Eczema Cream (4oz) - 72609-704-04

Drug Facts Active Ingredient

Colloidal Oatmeal 2.0%

Purpose

Skin Protectant

Uses

Temporarily protects and helps relieve minor skin irritation and itching due to eczema.

Warnings

- For external use only
- When using this product do not get into eyes

STOP USE

- If condition worsens, or if symptoms persist for more than 7 days or clear up and occur again within a few days,, discontinue use of this product and consult a doctor.
- Do not apply to wounds or damaged skin.
- Do not bandage tightly.

PREGNANCY OR BREAST FEEDING

If pregnant or breast-feeding, ask a health professional before use.

Keep out of reach of children.

If swallowed, get medical help or contact a Poison Control Center right away.

Directions

Adults and children 5 years and over apply gently to the affected area as needed. Not recommended for face.

Other information

Protect from excessive heat

Store at 20-25oC (68-77F)

Inactive Ingredients

Arnica montana flower extract, cetyl palmitate, ethylhexylglycerin, eucalyptus (Eucalyptus cinerea), glycerin, glyceryl stearate, jojoba (Buxus chinensis) oil, peppermint (mentha piperita) oil, phenoxyethanol, rosemary (Rosmariunus officinalis) oil, sodium citrate, stearic acid, sweet almond (Prunus amydgalus dulcis) oil, tea tree (Melaleuca alternifolia) oil, tocopherol (Vitamin E), water

Questions?

Call (866) 419-3567

Monday through Friday 8:00am - 2:00pm ET

Tamper evident: Do not use if safety seal under cap is broken or missing.

Manufactured for Smith Amish LLC 16350 N Hwy 329 Reddick, FL 32634

Label

Smith Amish Eczema Cream (72609-704-02)

Deep Moisturizing Cream

for sensitive, distressed, dry, scaly skin

Clean Fresh Scent

Easily Absorbed and Non-Greasy

Net wt. 2oz (59g)